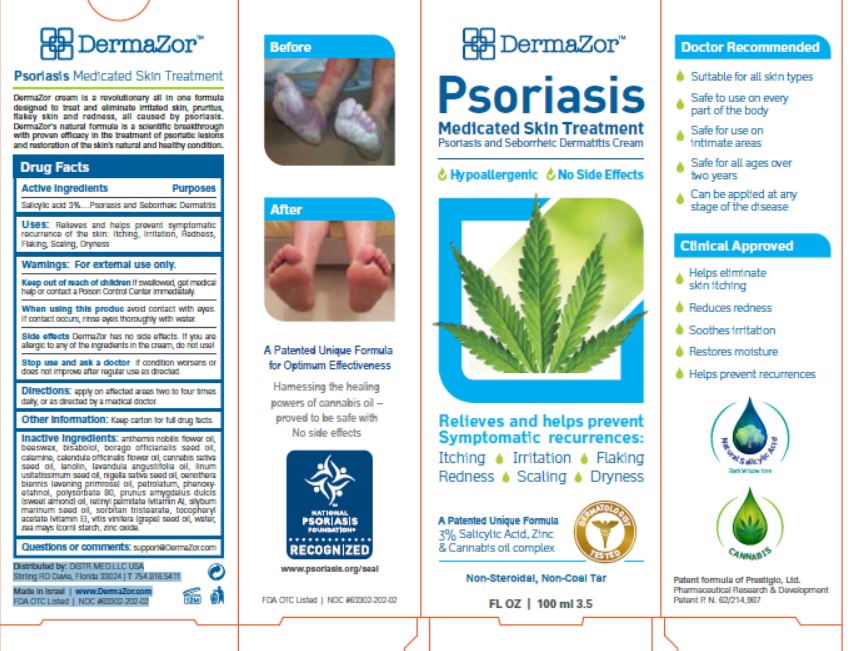 DRUG LABEL: Dermazor
NDC: 63302-202 | Form: CREAM
Manufacturer: PRESTIGIO LTD
Category: otc | Type: HUMAN OTC DRUG LABEL
Date: 20200116

ACTIVE INGREDIENTS: SALICYLIC ACID 3 g/100 g
INACTIVE INGREDIENTS: LANOLIN; PETROLATUM; WATER; ZINC OXIDE; STARCH, CORN; GRAPE SEED OIL; CANNABIS SATIVA SEED OIL; CALENDULA OFFICINALIS FLOWER; CHAMAEMELUM NOBILE FLOWER OIL; EVENING PRIMROSE OIL; WHITE WAX; POLYSORBATE 65; POLYSORBATE 80; SILYBUM MARIANUM SEED OIL; PHENOXYETHANOL; VITAMIN A; VITAMIN D; BORAGE SEED OIL; ALMOND OIL; LEVOMENOL; NIGELLA SATIVA SEED OIL; LAVENDER OIL

Drug Facts

Active Ingredients

Salicylic acid 3%

Purpose

Psoriasis and Seborrheic Dermatitis

Uses

Relieves and helps prevent symptomatic recurrence of the skin:

- Itching
- Irritation
- Redness
- Flaking
- Scaling
- Dryness

Warnings

For external use only.

Keep out of reach of children

If swallowed, get medical help or contact a Poison Control Center immediately.

When using this product

avoid contact with eyes. If contact occurs, rinse eyes thoroughly with water.

Stop use and ask a doctor if

condition worsens or does not improve after regular use as directed.

Side effects

DermaZor has no side effects. If you are allergic to any of the ingredients in the cream, do not use.

Directions

Apply to the affected areas two to four times daily or as directed by a medical doctor.

Other Information

Keep carton for full drug facts.

Inactive Ingredients

anthemis nobilis flower oil, beeswax, bisabolol, borago officianalis seed oil, calamine, calendula officinalis flower oil, cannabis sativa seed oil, lanolin, lavandula angustifolia oil, linum usitatissimum seed oil, nigella sativa seed oil, oenothera biennis (evening primrose) oil, petrolatum, phenoxyetahnol,
polysorbate 80, prunus amygdalus dulcis (sweet almond) oil, retinyl palmitate (vitamin A), silybum marinum seed oil, sorbitan tristearate, tocopheryl
acetate (vitamin E), vitis vinifera (grape) seed oil, water, zea mays (corn) starch, zinc oxide.

Questions or Comments:

support@DermaZor.com

Website: www.DermaZor.com

Distributed by: DISTR.MED.LLC USA
Stirling RD Davie, Florida 33024 | T 754.816.5411

Made in Israel | www.DermaZor.com
FDA OTC Listed | NDC #63302-202-02

Principal Display Panel

NDC: 63302-202-02

DermaZor Psoriasis

MEDICATED SKIN TREATMENT

Psoriasis and Seborrheic Dermatitis Cream

Hypoallergenic No Side Effects

Relieves and helps prevent Symptomatic recurrences:

- Itching
- Irritation
- Redness
- Flaking
- Scaling
- Dryness

A Patented Unique Formula

3% Salicylic Acid, Zinc and Cannabis Oil Complex

Non-Steroidal, Non-Coal Tar

FL OZ | 100 ml 3.5